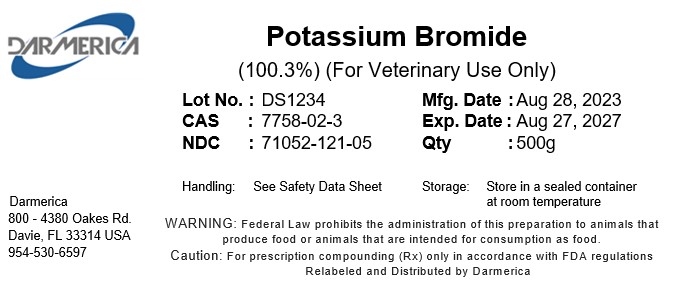 DRUG LABEL: Potassium Bromide
NDC: 71052-121 | Form: POWDER
Manufacturer: DARMERICA, LLC
Category: other | Type: BULK INGREDIENT - ANIMAL DRUG
Date: 20241223

ACTIVE INGREDIENTS: POTASSIUM BROMIDE 1 kg/1 kg

Potassium Bromide